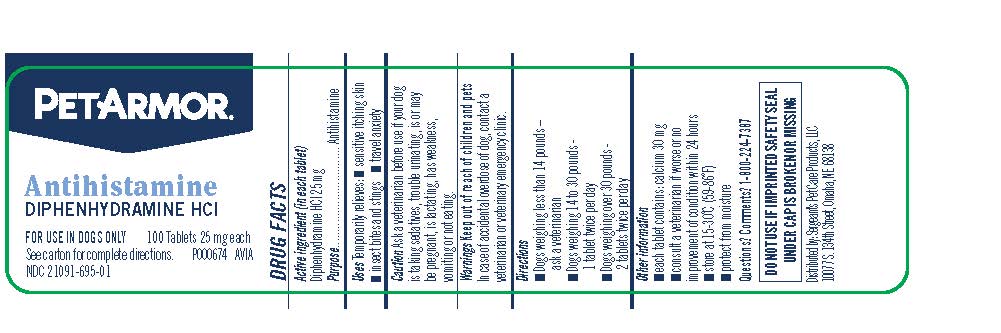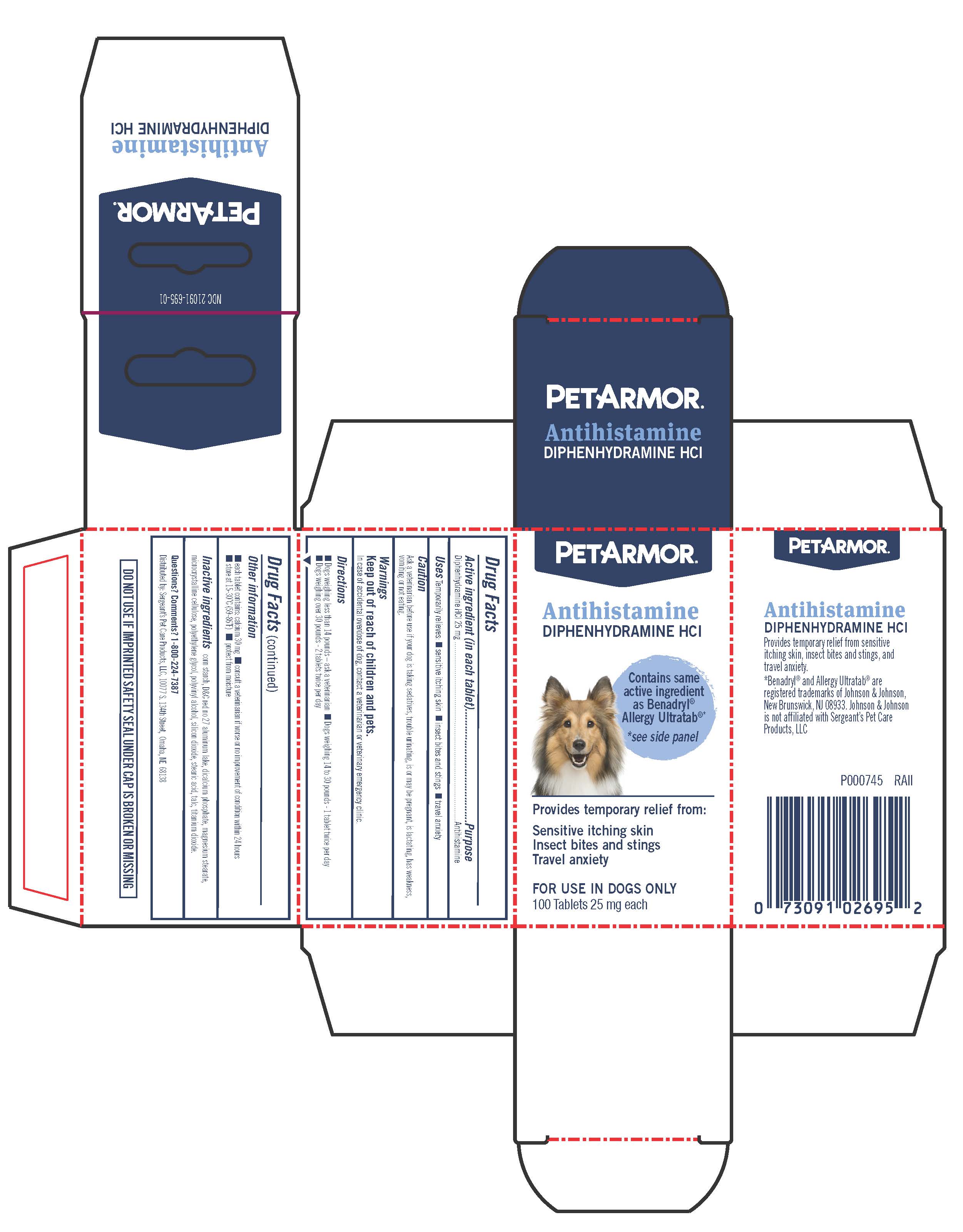 DRUG LABEL: Diphenhydramine HCL
NDC: 21091-695 | Form: TABLET, COATED
Manufacturer: Sergeants Pet Care Products LLC
Category: animal | Type: OTC ANIMAL DRUG LABEL
Date: 20230614

ACTIVE INGREDIENTS: DIPHENHYDRAMINE HYDROCHLORIDE 25 mg/1 1

Antihistamine
DIPHENHYDRAMINE HCI

Active ingredient (in each tablet)....... Purpose

Diphenhydramine HCl 25 mg ................ Antihistamine

INDICATIONS AND USAGE

Uses Temporarily relieves: ■ sensitive itching skin ■ insect bites and stings ■ travel anxiety

PRECAUTIONS

Caution
Ask a veterinarian before use if your dog is taking sedatives, trouble urinating, is or may be pregnant, is lactating, has weakness, vomiting or not eating.

Warnings
Keep out of reach of children and pets.
In case of accidental overdose of dog, contact a veterinarian or veterinary emergency clinic.

Directions

■ Dogs weighing less than 14 pounds – ask a veterinarian

■ Dogs weighing 14 to 30 pounds - 1 tablet twice per day

■ Dogs weighing over 30 pounds - 2 tablets twice per day

DO NOT USE IF IMPRINTED SAFETY SEAL UNDER CAP IS BROKEN OR MISSING

■ each tablet contains: calcium 30 mg ■ consult a veterinarian if worse or no improvement of condition within 24 hours ■ store at 15-30˚C (59-86˚F) ■ protect from moisture

INACTIVE INGREDIENT

corn starch, D&C red no 27 aluminum lake, dicalcium phosphate, magnesium stearate, microcrystalline cellulose, polyethylene glycol, polyvinyl alcohol, silicon dioxide, stearic acid, talc, titanium dioxide.

Questions? Comments? 1-800-224-7387